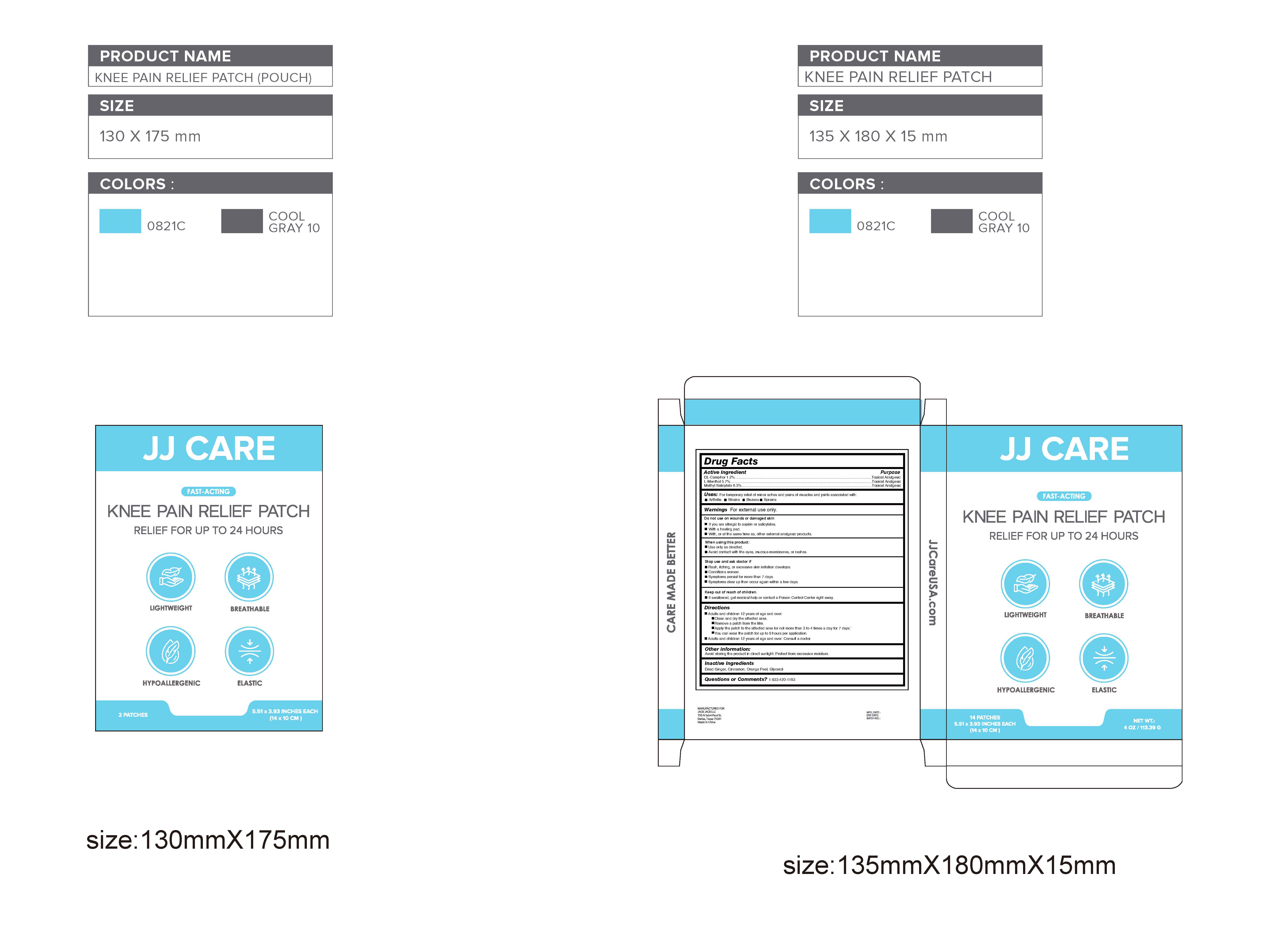 DRUG LABEL: Knee Pain Relief Patch
NDC: 81484-401 | Form: PATCH
Manufacturer: Anhui Miao De Tang Pharmaceutical Co., Ltd.
Category: otc | Type: HUMAN OTC DRUG LABEL
Date: 20231114

ACTIVE INGREDIENTS: METHYL SALICYLATE 0.189 g/1 1; MENTHOL 0.171 g/1 1; CAMPHOR (SYNTHETIC) 0.036 g/1 1
INACTIVE INGREDIENTS: GINGER OIL; CINNAMON; GLYCERIN; ORANGE PEEL

Knee Pain Relief Patch

Knee Pain Relief Patch

ACTIVE INGREDIENT

DL-Camphor 1.2% / Topical Analgesic

L-Menthol 5.7% / Topical Analgesic

Methyl Salicylate6.3% / Topical Analgesic

PURPOSE

Topical Analgesic,Knee Pain Relief Patch

INDICATIONS AND USAGE

For temporary relief of minor aches and pains of muscles and joints associated with:Arthritis,Strains,Bruises,Sprains

WARNINGS

For external use only.

Do not use on wounds or damaged skin
If you are allergic to aspirin or salicylates.
With a heating pad.
With, or at the same time as, other external analgesic products.

When using this product:

Use only as directed.
Avoid contact with the eyes, mucous membranes, or rashes.

STOP USE

Rash, itching, or excessive skin irritation develops.

Conditions worsen.
Symptoms persist for more than 7 days.
Symptoms clear up then occur again within a few days.

Keep out of reach of children.If swallowed, get medical help or contact a Poison Control Center right away.

DOSAGE AND ADMINISTRATION

Adults and children 12 years of age and over:
Clean and dry the affected area.
Remove a patch from the film.
Apply the patch to the affected area for not more than 3 to 4 times a day for 7 days.`
You can wear the patch for up to 8 hours per application.
Consult a doctor

STORAGE AND HANDLING

Avoid storing the product in direct sunlight. Protect from excessive moisture.

INACTIVE INGREDIENT

Dried Ginger, Cinnamon, Orange Peel, Glycerol